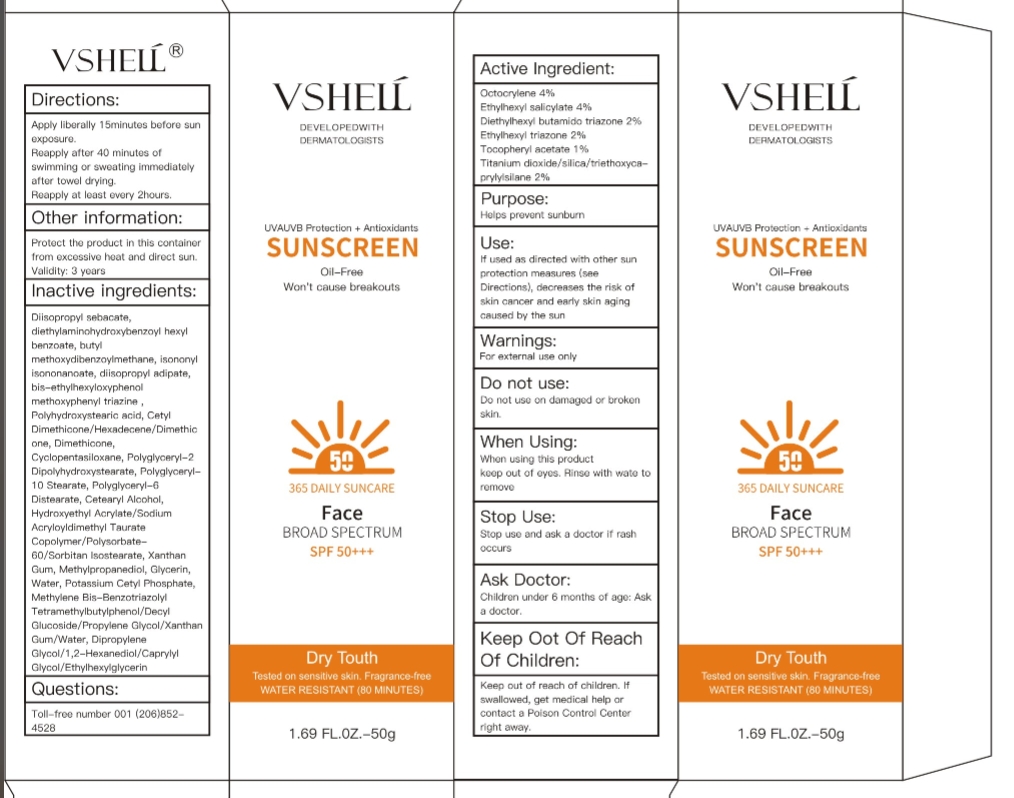 DRUG LABEL: VSHELL sunscreen
NDC: 84507-001 | Form: CREAM
Manufacturer: Guangdong Miaolian Cosmetics Co., Ltd.
Category: otc | Type: HUMAN OTC DRUG LABEL
Date: 20240710

ACTIVE INGREDIENTS: ISCOTRIZINOL 2 g/100 mL; OCTISALATE 4 g/100 mL; TITANIUM DIOXIDE 2 g/100 mL; TOCOTRIENOLS 1 g/100 mL; OCTOCRYLENE 4 g/100 mL; ETHYLHEXYL TRIAZONE 2 g/100 mL
INACTIVE INGREDIENTS: DIISOPROPYL SEBACATE; METHYLPROPANEDIOL; XANTHAN GUM; POLYGLYCERYL-6 DISTEARATE; HYDROXYETHYL ACRYLATE/SODIUM ACRYLOYLDIMETHYL TAURATE COPOLYMER (45000 MPA.S AT 1%); WATER; ISONONYL ISONONANOATE; GLYCERIN; DIMETHICONE; BEMOTRIZINOL; POLYHYDROXYSTEARIC ACID (2300 MW); POLYGLYCERYL-2 DIPOLYHYDROXYSTEARATE; CYCLOMETHICONE 5; DIETHYLAMINO HYDROXYBENZOYL HEXYL BENZOATE; AVOBENZONE; DIISOPROPYL ADIPATE; 1-HEXADECENE; POLYGLYCERYL-10 STEARATE; CETOSTEARYL ALCOHOL; POTASSIUM CETYL PHOSPHATE; DIPROPYLENE GLYCOL; BISOCTRIZOLE

SUNSCREEN PACKAGE

uses

1.Active Ingredient: Octocrylene 4%
Ethylhexyl salicylate 4%
Diethylhexyl butamido triazone 2%
Ethylhexyl triazone 2%
Tocopheryl acetate 1%
Titanium dioxide/silica/triethoxycaprylylsilane 2%
2.Purpose: Helps prevent sunburn
3.Use: If used as directed with other sun protection measures (see Directions), decreases the risk of skin cancer and early skin aging caused by the sun.
4.Warnings: For external use only
5.Do not use: Do not use on damaged or broken skin.
6.When Using : When using this product
keep out of eyes. Rinse with wate to remove
Stop use and ask doctor if rash occurs.
7.Stop Use : Stop use and ask a doctor if rash occurs
8.Ask Doctor: Children under 6 months of age: Ask a doctor.
9.Keep Oot Of Reach Of Children
: Keep out of reach of children. If swallowed, get medical help or contact a Poison Control Center right away.
10.Directions: Apply liberally 15minutes before sun exposure.
Reapply after 40 minutes of swimming or sweating immediately after towel drying.
Reapply at least every 2hours.
11.Other information: Protect the product in this container from excessive heat and direct sun.
Validity: 3 years
12.Inactive ingredients: Diisopropyl sebacate, diethylaminohydroxybenzoyl hexyl benzoate, butyl methoxydibenzoylmethane, isononyl isononanoate, diisopropyl adipate, bis-ethylhexyloxyphenol methoxyphenyl triazine , Polyhydroxystearic acid, Cetyl Dimethicone/Hexadecene/Dimethicone, Dimethicone, Cyclopentasiloxane, Polyglyceryl-2 Dipolyhydroxystearate, Polyglyceryl-10 Stearate, Polyglyceryl-6 Distearate, Cetearyl Alcohol, Hydroxyethyl Acrylate/Sodium Acryloyldimethyl Taurate Copolymer/Polysorbate-60/Sorbitan Isostearate, Xanthan Gum, Methylpropanediol, Glycerin, Water, Potassium Cetyl Phosphate, Methylene Bis-Benzotriazolyl Tetramethylbutylphenol/Decyl Glucoside/Propylene Glycol/Xanthan Gum/Water, Dipropylene Glycol/1,2-Hexanediol/Caprylyl Glycol/Ethylhexylglycerin
13.Questions: Toll-free number 001 (206)852-4528